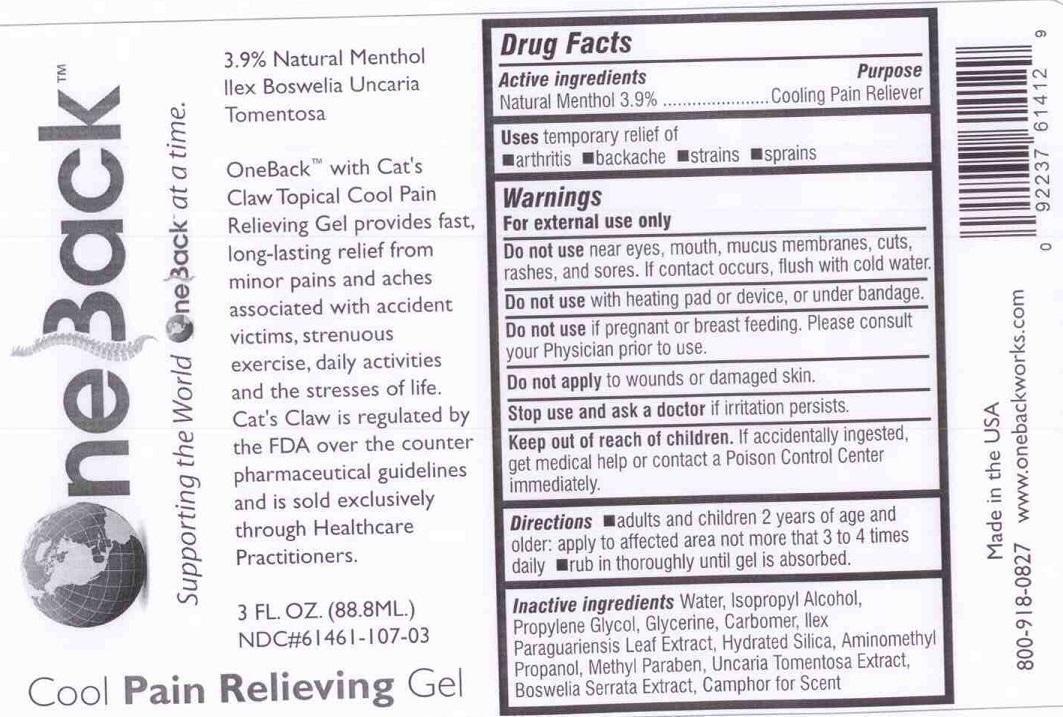 DRUG LABEL: ONEBACK
NDC: 69643-101 | Form: GEL
Manufacturer: WORLD WIDE MEDICAL SERVICES, INC.
Category: otc | Type: HUMAN OTC DRUG LABEL
Date: 20150430

ACTIVE INGREDIENTS: MENTHOL 3.9 g/100 mL
INACTIVE INGREDIENTS: WATER; ISOPROPYL ALCOHOL; PROPYLENE GLYCOL; GLYCERIN; CARBOMER 940; ILEX PARAGUARIENSIS LEAF; HYDRATED SILICA; AMINOMETHYLPROPANOL; METHYLPARABEN; UNCARIA TOMENTOSA LEAF; BOSWELLIA SERRATA RESIN OIL; CAMPHOR OIL

ACTIVE INGREDIENTS

NATURAL MENTHOL 3.9%

PURPOSE

COOLING PAIN RELIEF

USES

TEMPORARY RELIEF OF

- ARTHRITIS
- BACKACHE
- STRAINS
- SPRAINS

WARNINGS

FOR EXTERNAL USE ONLY

DO NOT USE NEAR EYES, MOUTH, MUCUS MEMBRANES, CUTS, RASHES, AND SORES. IF CONTACT OCCURS, FLUSH WITH COLD WATER.

DO NOT USE WITH HEATING PAD OR DEVICE, OR UNDER BANDAGE.

DO NOT USE IF PREGNANT OR BREAST FEEDING. PLEASE CONSULT YOUR PHYSICIAN PRIOR TO USE.

DO NOT APPLY TO WOUNDS OR DAMAGED SKIN.

STOP USE AND ASK A DOCTOR IF IRRITATION PERSISTS.

KEEP OUT OF REACH OF CHILDREN. IF ACCIDENTALLY INGESTED, GET MEDICAL HELP OR CONTACT A POISON CONTROL CENTER IMMEDIATELY.

DIRECTIONS

- ADULTS AND CHILDREN 2 YEARS OF AGE AND OLDER: APPLY TO AFFECTED AREA NOT MORE THAN 3 TO 4 TIMES DAILY
- RUB IN THOROUGHLY UNTIL IT IS ABSORBED.

INACTIVE INGREDIENTS

WATER, ISOPROPYL ALCOHOL, PROPYLENE GLYCOL, GLYCERINE, CARBOMER, ILEX PARAGUARIENSIS LEAF EXTRACT, HYDRATED SILICA, AMINOMETHYL PROPANOL, METHYL PARABEN, UNCARIA TOMENTOSA EXTRACT, BOSWEILA SERRATA EXTRACT, CAMPHOR FOR SCENT